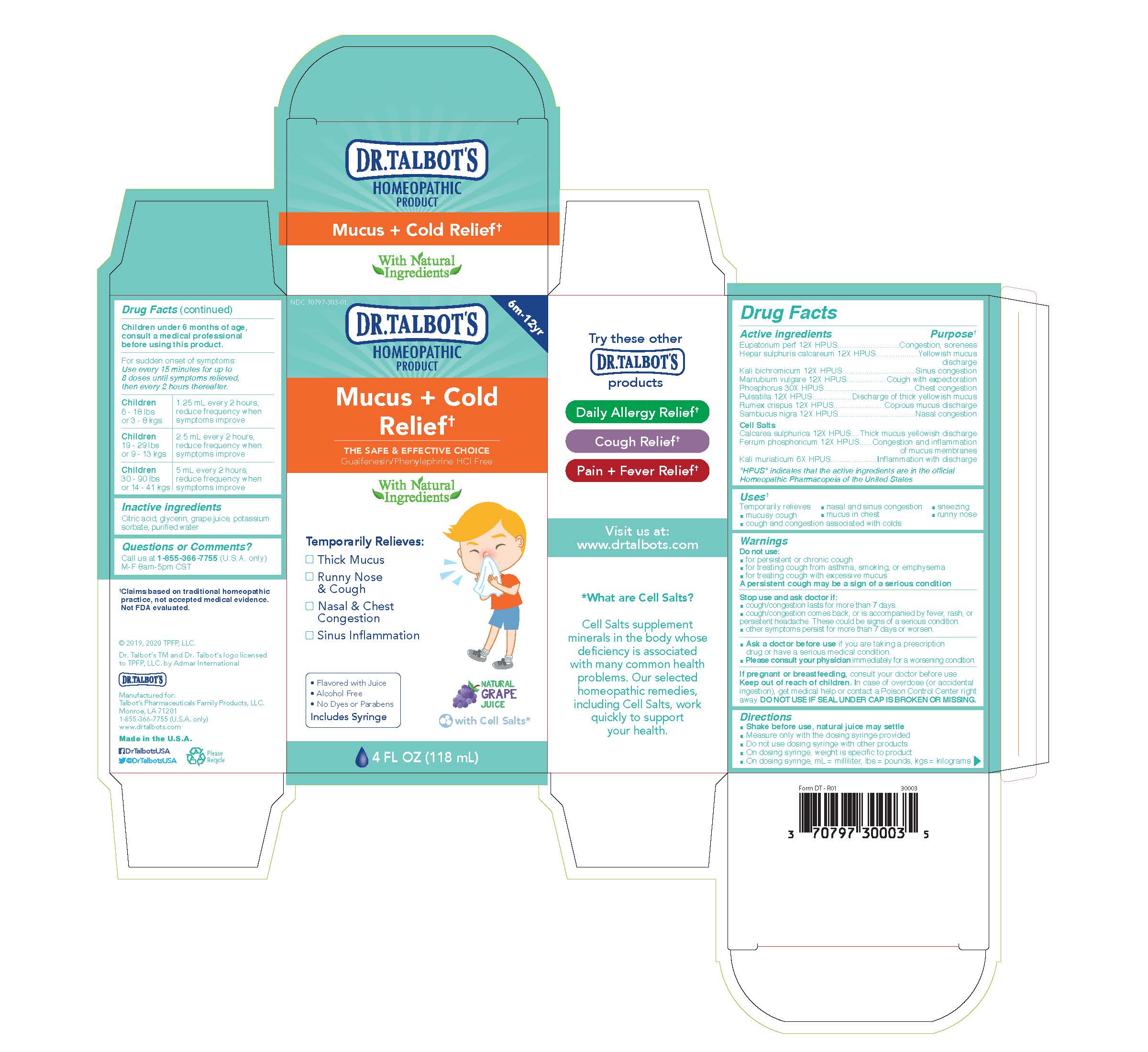 DRUG LABEL: Dr. Talbots Mucus Cold Relief
NDC: 70797-313 | Form: LIQUID
Manufacturer: Talbot's Pharmaceuticals Family Products, LLC.
Category: homeopathic | Type: HUMAN OTC DRUG LABEL
Date: 20211005

ACTIVE INGREDIENTS: EUPATORIUM PERFOLIATUM FLOWERING TOP 12 [hp_X]/118 mL; SAMBUCUS NIGRA FLOWERING TOP 12 [hp_X]/118 mL; CALCIUM SULFATE ANHYDROUS 12 [hp_X]/118 mL; POTASSIUM CHLORIDE 6 [hp_X]/118 mL; MARRUBIUM VULGARE 12 [hp_X]/118 mL; PHOSPHORUS 30 [hp_X]/118 mL; RUMEX CRISPUS ROOT 12 [hp_X]/118 mL; FERROSOFERRIC PHOSPHATE 12 [hp_X]/118 mL; CALCIUM SULFIDE 12 [hp_X]/118 mL; POTASSIUM DICHROMATE 12 [hp_X]/118 mL; ANEMONE PULSATILLA 12 [hp_X]/118 mL
INACTIVE INGREDIENTS: CONCORD GRAPE JUICE; POTASSIUM SORBATE; WATER; GLYCERIN; CITRIC ACID MONOHYDRATE

Active Ingredients

Eupatorium perf 12X HPUS
Hepar sulphuris calcareum 12X HPUS
Kali bichromicum 12X HPUS
Marrubium vulgare 12X HPUS
Phosphorus 30X HPUS
Pulsatilla 12X HPUS
Rumex crispus 12X HPUS
Sambucus nigra 12x HPUS
Cell Salts
Calcarea sulphurica 12X HPUS
Ferrum phosphoricum 12X HPUS
Kali muriaticum 6X HPUS

Purpose

Congestion, soreness
Yellowish mucus discharge

Sinus congestion
Cough with expectoration
Chest congestion
Discharge of thick yellowish mucus
Copious mucus discharge
Nasal congestion
Thick mucus yellowish discharges
Congestion and inflammation of mucus membranes
Inflammation with discharge

Uses

Temporarily relieves

- mucusy cough
- cough and congestion associated with colds
- nasal and sinus congestion
- mucus in chest
- sneezing
- runny nose

Warnings

Do not use:

- for persistent or chronic cough
- for treating cough from asthma, smoking, or emphysema
- for treating cough with excessive mucus

A persistent cough may be a sign of a serious condition

Stop use and ask doctor if:

- cough/congestion lasts for more than 7 days.
- cough/congestion comes back, or is accompanied by fever, rash, or persistent headache. These could be signs of a serious confition.
- other symptoms persist for more than 7 days or worsen
- Ask a doctor before use if you are taking a prescription drug or have a serious medical condition.
- Please consult your physician immediately for a worsening condition.

Pregnancy or breastfeeding

If pregnant or breastfeeding, consult your doctor before use.

Keep out of reach of children. In case of overdoes (or accidental ingestion), get medical help or contact a Poison Control Center right away. DO NOT USE IF SEAL UNDER CAP IS BROKEN OR MISSING.

Directions

- Shake before use, natural juice may settle
- Measure only with the dosing syringe provided
- Do not use dosing syringe with other products
- On dosing syringe, weight is specific to product
- On dosing syringe, ml = milliliter, lbs = pounds, kgs = kilograms

Children under 6 months of age, consult a medical professional before using this product.

For sudden onset of symptoms: Use every 15 minutes for up to 8 doses until symptoms relieved, then every 2 hours thereafter.

Children 6 - 18 lbs or 3 - 8 kgs

1.25 ml every 2 hours, reduce frequency when symptoms improve

Children 19 - 29 lbs or 9 - 13 kgs

2.5 ml every 2 hours, reduce frequency when symptoms improve

Children 30 - 90 lbs or 14 - 41 kgs

5 ml every 2 hours, reduce frequency when symptoms improve

Inactive Ingredients

Citric acid, glycerin, grape juice, potassium sorbate, purified water

Questions

Questions or Comments?

Call us at 1-800-588-6227

M-F 8am-5pm CST